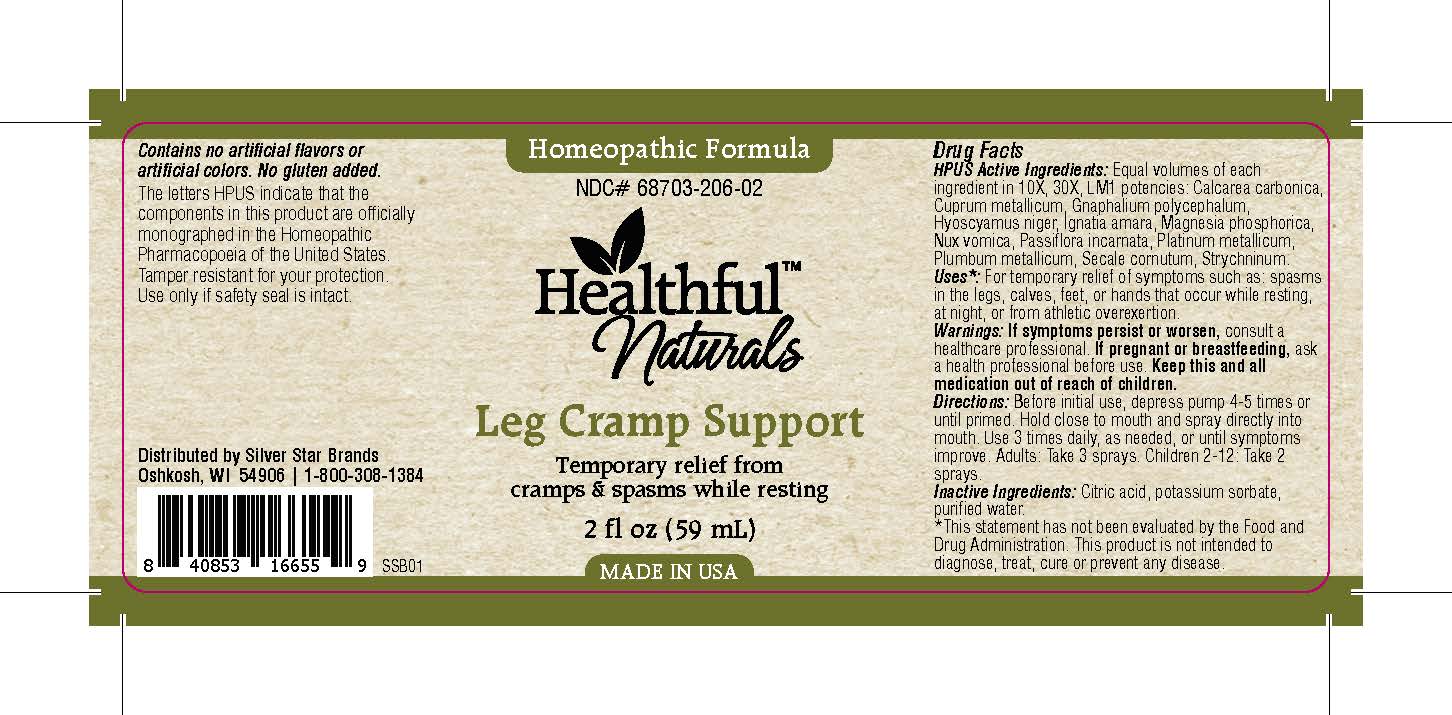 DRUG LABEL: Leg Cramp Support
NDC: 68703-206 | Form: SPRAY
Manufacturer: Silver Star Brands
Category: homeopathic | Type: HUMAN OTC DRUG LABEL
Date: 20151110

ACTIVE INGREDIENTS: PSEUDOGNAPHALIUM OBTUSIFOLIUM 10 [hp_X]/59 mL; COPPER 10 [hp_X]/59 mL; PLATINUM 10 [hp_X]/59 mL; CLAVICEPS PURPUREA SCLEROTIUM 10 [hp_X]/59 mL; STRYCHNOS IGNATII SEED 10 [hp_X]/59 mL; MAGNESIUM PHOSPHATE, DIBASIC TRIHYDRATE 10 [hp_X]/59 mL; STRYCHNOS NUX-VOMICA SEED 10 [hp_X]/59 mL; PASSIFLORA INCARNATA FLOWERING TOP 10 [hp_X]/59 mL; LEAD 10 [hp_X]/59 mL; STRYCHNINE 10 [hp_X]/59 mL; OYSTER SHELL CALCIUM CARBONATE, CRUDE 10 [hp_X]/59 mL; HYOSCYAMUS NIGER 10 [hp_X]/59 mL
INACTIVE INGREDIENTS: ANHYDROUS CITRIC ACID; POTASSIUM SORBATE; WATER

Healthful™ Naturals Leg Cramp Support

HPUS Active Ingredients

Equal volumes of each ingredient in 10X, 30X, LM1 potencies: Calcarea carbonica, Cuprum metallicum, Gnaphalium polycephalum, Hyoscyamus niger, Ignatia amara, Magnesia phosphorica, Nux vomica, Passiflora incarnata, Platinum metallicum, Plumbum metallicum, Secale cornutum, Strychninum.

Uses

*For temporary relief of symptoms such as: spasms in the legs, calves, feet, or hands that occur while resting, at night, or from athletic overexertion.

*This statement has not been evaluated by the Food and Drug Administration. This product is not intended to diagnose, treat, cure or prevent any disease.

Warnings

If symptoms persist or worsen, consult a healthcare professional. If pregnant or breastfeeding, ask a health professional before use. Keep this and all medication out of reach of children.

Directions

Before initial use, depress pump 4-5 times or until primed. Hold close to mouth and spray directly into mouth. Use 3 times daily, as needed, or until symptoms improve. Adults: Take 3 sprays. Children 2-12: Take 2 sprays.

Other Information

Contains no artificial flavors or artificial colors. No gluten added. The letters HPUS indicate that the components in this product are officially monographed in the Homeopathic Pharmacopoeia of the United States. Tamper resistant for your protection. Use only if safety seal is intact.

INACTIVE INGREDIENT

Citric acid, potassium sorbate, purified water.

KEEP OUT OF REACH OF CHILDREN

Keep this and all medication out of reach of children.

PREGNANCY OR BREAST FEEDING

If pregnant or breastfeeding, ask a health professional before use.

PURPOSE

Temporary relief from cramps & spasms while resting